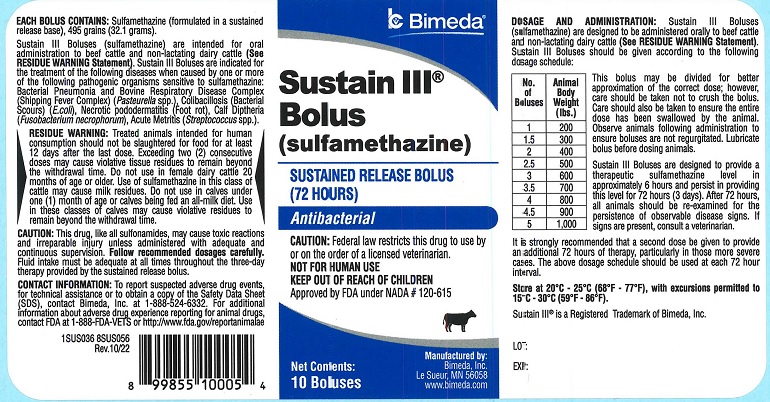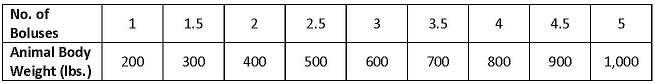 DRUG LABEL: Sustain III 
NDC: 61133-1331 | Form: TABLET
Manufacturer: Bimeda, Inc.
Category: animal | Type: PRESCRIPTION ANIMAL DRUG LABEL
Date: 20240328

ACTIVE INGREDIENTS: Sulfamethazine 32.1 g/1 1

DESCRIPTION

Sustain III® Bolus
(sulfamethazine)

SUSTAINED RELEASED BOLUS (72 HOURS)

Antibacterial

CAUTION: Federal law restricts this drug to use by or on the order of a licensed veterinarian.

NOT FOR HUMAN USE
KEEP OUT OF REACH OF CHILDREN

Approved by FDA under NADA # 120-615

INDICATIONS AND USAGE

EACH BOLUS CONTAINS: Sulfamethazine (formulated in a sustained release base), 495 grains (32.1 grams).

Sustain III Boluses (sulfamethazine) are intended for oral administration to beef cattle and non-lactating dairy cattle (See RESIDUE WARNING Statement). Sustain III Boluses are indicated for the treatment of the following diseases when caused by one or more of the following pathogenic organisms sensitive to sulfamethazine: Bacterial Pneumonia and Bovine Respiratory Disease Complex (Shipping Fever Complex) (Pasteurella spp.), Colibacillosis (Bacterial Scours) (E. coli), Necrotic pododermatitis (Foot rot), Calf Diphtheria (Fusobacterium necrophorum), Acute Metritis (Streptococcusspp.).

RESIDUE WARNING

RESIDUE WARNING: Treated animals intended for human consumption should not be slaughtered for food for at least 12 days after the last dose. Exceeding two (2) consecutive doses may cause violative tissue residues to remain beyond the withdrawal time. Do not use in female dairy cattle 20 months of age or older. Use of sulfamethazine in this class of cattle may cause milk residues. Do not use in calves under one (1) month of age or calves being fed an all milk diet. Use in these classes of calves may cause violative residues to remain beyond the withdrawal time.

PRECAUTIONS

CAUTION: This drug, like all sulfonamides, may cause toxic reactions and irreparable injury unless administered with adequate and continuous supervision. Follow recommended dosages carefully. Fluid intake must be adequate at all times throughout the three-day therapy provided by the sustained release bolus. This product has not been shown to be effective for non-ruminating calves.

CONTACT INFORMATION: To report adverse drug events, for technical assistance or to obtain a copy of the Safety Data Sheet (SDS), contact Bimeda, Inc. at 1-888-524-6332. For additional information about adverse drug experience reporting for animal drugs, contact FDA at 1-888-FDA-VETS or http://www.fda.gov/reportanimalae

DOSAGE AND ADMINISTRATION: Sustain III Boluses (sulfamethazine) are designed to be administered orally to beef cattle and non-lactating dairy cattle (See RESIDUE WARNING Statement). Sustain III Boluses should be given according to the following dosage schedule:

This bolus may be divided for better approximation of correct dose; however, care should be taken not to crush the bolus. Care should also be taken to ensure the entire dose has been swallowed by the animal. Observe animals following administration to ensure boluses are not regurgitated. Lubricate bolus before dosing animals.

Sustain III Boluses are designed to provide a therapeutic sulfamethazine level in approximately 6 hours and persist in providing this level for 72 hours (3 days). After 72 hours, all animals should be re-examined for persistence of observable disease signs. If signs are present, consult a veterinarian. It is strongly recommended that a second dose be given to provide for an additional 72 hours of therapy, particularly in those more severe cases. The dosage schedule should be used at each 72 hour interval.

STORAGE AND HANDLING

Store at 20°C - 25°C (68°F - 77°F), with excursions permitted to 15°C - 30°C (59°F - 86°F).